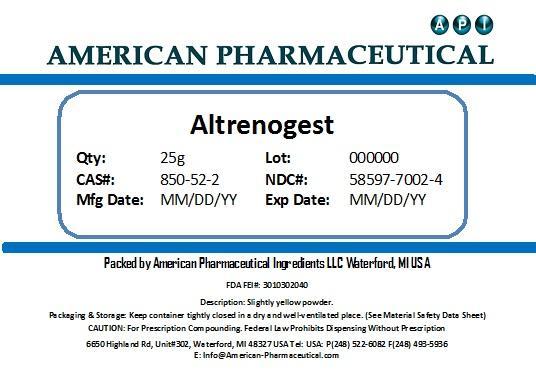 DRUG LABEL: Altrenogest
NDC: 58597-7002 | Form: POWDER
Manufacturer: AMERICAN PHARMACEUTICAL INGREDIENTS LLC
Category: other | Type: BULK INGREDIENT
Date: 20131031

ACTIVE INGREDIENTS: ALTRENOGEST 1 g/1 g

Altrenogest